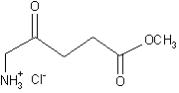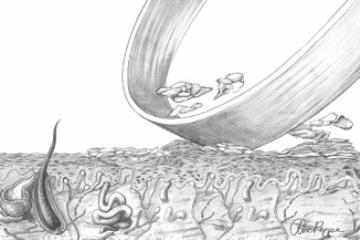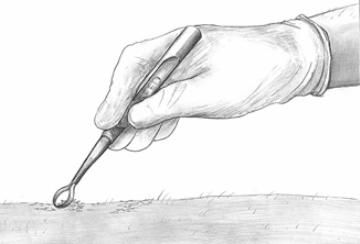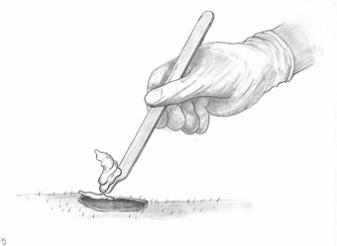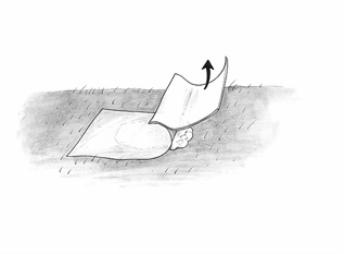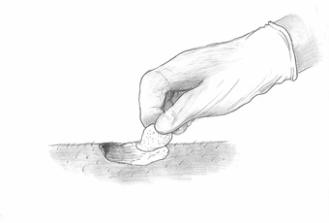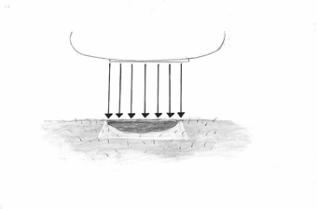 DRUG LABEL: Unknown
Manufacturer: Penn Pharmaceutical Services Ltd.
Category: prescription | Type: Human Prescription Drug Label
Date: 20070926

METVIXIA™ (methyl aminolevulinate) Cream, 16.8%
For Topical Use Only.
Not for Ophthalmic, Oral, or Intravaginal Use
Must be dispensed to and applied by a physician.

DESCRIPTION

Metvixia Cream is an oil in water emulsion. Metvixia Cream contains methyl aminolevulinate hydrochloride equivalent to168 mg/g of methyl aminolevulinate.

Methyl aminolevulinate hydrochloride is a white to slightly yellow powder that is freely soluble in water and methanol, soluble in ethanol and practically insoluble in most organic solvents.

The chemical formula for methyl aminolevulinate HCl is C6H11NO3·HCl (MW=181.62) and it has the following structural formula:

Metvixia Cream contains glyceryl monostearate, cetostearyl alcohol, polyoxyl stearate, cholesterol and oleyl alcohol as emulsifying agents. It also contains glycerin, white petrolatum, isopropyl myristate, refined peanut oil, refined almond oil as emollients, edetate disodium as a chelating agent and methylparaben and propylparaben as preservatives.

CLINICAL PHARMACOLOGY

Mechanism of Action

Photosensitization following application of Metvixia Cream occurs through the metabolic conversion of methyl aminolevulinate (prodrug) to photoactive porphyrins (PAP), which accumulates in the skin lesions to which Metvixia Cream has been applied. When exposed to light of appropriate wavelength and energy, the accumulated photoactive porphyrins produce a photodynamic reaction, resulting in a cytotoxic process dependent upon the simultaneous presence of oxygen. The absorption of light results in an excited state of porphyrin molecules, and subsequent spin transfer from photoactive porphyrins to molecular oxygen generates singlet oxygen, which can further react to form superoxide and hydroxyl radicals. Photosensitization of actinic (solar) keratosis lesions using Metvixia Cream, plus illumination with a CureLight BroadBand Model CureLight 01 (a red light of 570 to 670 nm wavelength) at 75 J/cm^2, is the basis for Metvixia photodynamic therapy (PDT).

Pharmacokinetics

The time-course of PAPs after application of Metvixia Cream has been monitored by means of fluorescence. After application of Metvixia Cream to actinic keratosis lesions in 8 patients, fluorescence was measured at several time points over 28 hours. Three hours after the application of Metvixia Cream the fluorescence in the treated lesions was significantly greater than that seen in both treated and untreated normal skin, and after application of vehicle cream (not containing methyl aminolevulinate) to normal skin. After application of Metvixia Cream for 28 hours and subsequent illumination with red light of 570 to 670 nm wavelength at a total light dose of 75 J/cm^2, complete photobleaching (photodegradation) of Protoporphyrin IX occurred with levels of Protoporphyrin IX returning to pre-treatment values within 1 hour after illumination. However, the fate of other photoactive porphyrins are unknown.

The clinical dose of methyl aminolevulinate cream and duration of application were derived from a study in which three different strengths of the cream (16, 80 and 160 mg/g methyl aminolevulinate, as hydrochloride), each applied for 3 hours or 18 hours, were tested in 16 patients.

CLINICAL STUDIES

Metvixia Cream plus illumination with the CureLight BroadBand Model CureLight 01 (a red light of 570 to 670 nm wavelength) at 75 J/cm^2 has been studied in 130 patients with non-hyperkeratotic actinic keratoses in two clinical trials. These trials were not identical; however, both were randomized, multicenter, and double-blinded with patients randomized to Metvixia-PDT and Vehicle-PDT study arms that required two treatment sessions (7 days apart). One study was conducted in the U.S. and patients were randomized 1:1 Metvixia to Vehicle and one study was conducted in Australia with patients randomized 4:1 Metvixia to Vehicle. In both studies treatment consisted of a multi-step process that was repeated after 7 days consisting of 1) Lesion preparation (debridement with sharp curette) to roughen the surface of the lesion. 2) Metvixia or Vehicle Cream application to lesions with occlusion with an adhesive, non-absorbent dressing, 3) Waiting at least 2.5 hours, but no more than 4 hours to allow for conversion of the methyl aminolevulinate, 4) Removal of cream with gauze and saline, 5) Red light Dosimetry and Illumination with the CureLight BroadBand Model CureLight 01 (a red light of 570 to 670 nm wavelength).

Study patients had previously untreated facial and scalp actinic keratoses (AKs) that were slightly palpable (better felt than seen). Hyperkeratotic actinic keratoses were excluded. In the U.S. study 100% of patients had 4 to 10 lesions at baseline. However, in the Australian study, 63% (70/111) of patients had less than 4 lesions at baseline, 31% (34/111) of the enrolled patients had 4 to 10 lesions, and 6% (7/111) had more than 10 lesions at baseline (a maximum of 6 treatment fields were allowed in this study).

A “Cleared” AK lesion was defined as being not visible and not palpable as assessed 3 months after the second treatment session. Patients with all treated lesions cleared at 3 months were defined as Complete Responders.

The percentage of patients in whom 75% or more of the treated lesions were clear and the percent of patients in whom 100% of the treated lesions were clear 3 months after the second Metvixia-PDT treatment session are shown in Table 1 for each of the two studies.

Table 1. Patient Responses at 3-Month Post-Second Treatment Session
 | Australian Study |  | U. S. Study
Patient Response | Metvixia-PDT | Vehicle PDT | Metvixia -PDT | Vehicle PDT
Patients with at least 75% of AK Lesions Cleared | 76/88 (86%) | 4/23 (17%) | 35/42 (83%) | 12/38 (32%)
Complete Responders (All Lesions clinically cleared at 3 months) | 71/88 (81%) | 3/23 (13%) | 33/42 (79%) | 8/38 (21%)

Patients with 4 or more lesions had lower success rates than those with less than 4 lesions when treated with PDT using Metvixia Cream (see Table 2).

Table 2. Complete Responders at 3-Month Post-Treatment for Different Baseline AK Lesion Counts
 | Australian Study |  | U.S. Study
Baseline Lesion Count | Metvixia-PDT | Vehicle PDT | Metvixia-PDT | Vehicle PDT
Below 4 | 49/55 (89%) | 3/15 (20%) | N/A | N/A
4 – 10 | 18/27 (67%) | 0/7 | 33/42 (79%) | 8/38 (21%)
More than 10 | 4/6 (67%) | 0/1 | N/A | N/A
Total | 71/88 (81%) | 3/23 (13%) | 33/42 (79%) | 8/38 (21%)

Lesions that were slightly palpable (Grade 1) had a better success rate than lesions that were visible and palpable (Grade 2) – See Table 3.

Table 3. Lesion Complete Response at 3-Month Post-Treatment for Different Lesion Grades
 | Australian Study |  | U.S. Study
Lesion Grade | Metvixia-PDT | Vehicle PDT | Metvixia-PDT | Vehicle PDT
Lesion Grade 1 (slightly palpable AK: better felt than seen) | 198/209 (95%) | 12/35 (34%) | 172/196 (88%) | 72/162 (44%)
Lesion Grade 2 (visible and palpable AK: easily seen and felt) | 119/151 (79%) | 9/39 (23%) | 49/64 (77%) | 20/80 (25%)
Total | 317/360 (88%) | 21/74 (28%) | 221/260 (85%) | 92/242 (38%)

Response rate by lesion location is presented in Table 4.

Table 4. Lesion Complete Response at 3-Month Post-Treatment for Different Lesion Locations
 | Australian Study |  | U.S. Study
Lesion Location | Metvixia-PDT | Vehicle PDT | Metvixia-PDT | Vehicle PDT
Face | 251/273 (92%) | 15/62 (24%) | 195/226 (86%) | 73/204 (36%)
Scalp | 66/87 (76%) | 6/12 (50%) | 26/34 (76%) | 19/38 (50%)
Total | 317/360 (88%) | 21/74 (28%) | 221/260 (85%) | 92/242 (38%)

The overall treatment effect as evidenced by the high vehicle response rate may include the contribution of lesion preparation, i.e. curettage. Adequate lesion preparation is an important component for AK therapy with Metvixia Cream.

Information regarding further treatments for residual or new AK lesions performed after 3 months is not available.

INDICATIONS AND USAGE

Metvixia Cream in combination with 570 to 670 nm wavelength red light illumination using the CureLight BroadBand Model CureLight 01 lamp is indicated for treatment of non-hyperkeratotic actinic keratoses of the face and scalp in immunocompetent patients when used in conjunction with lesion preparation (debridement using a sharp dermal curette) in the physician’s office when other therapies are unacceptable or considered medically less appropriate.

CONTRAINDICATIONS

Metvixia Cream is contraindicated in patients with cutaneous photosensitivity, or known allergies to porphyrins, and in patients with known sensitivities to any of the components of Metvixia Cream, which includes peanut and almond oil (See WARNINGS regarding sensitivity to Metvixia Cream).

This product contains refined peanut oil (See PRECAUTIONS).

WARNINGS

Metvixia Cream is intended for topical use in the physician’s office by trained physicians only. Do not apply to the eyes or to mucous membranes.

Metvixia Cream has demonstrated a high rate of contact sensitization (allergenicity) (See ADVERSE REACTIONS). Care should be taken by the physician applying Metvixia Cream to avoid inadvertent skin contact. Nitrile gloves should be worn when applying and removing the cream. Vinyl and latex gloves do not provide adequate protection when using this product.

Metvixia Cream when used with CureLight BroadBand Model CureLight 01 lamp must be used with appropriate protective sleeves obtained from the product manufacturer to decrease the risk of blood-borne transmitted diseases (hepatitis, HIV, etc.). Change the disposable covers for the device (probe and horseshoe positioning device) between patients. Universal Precautions should be used with this treatment.

PRECAUTIONS

The safety and efficacy have not been established for the treatment of cutaneous malignancies and for skin lesions other than non-hyperkeratotic face and scalp actinic keratoses using PDT with Metvixia Cream. Thick (hyperkeratotic) actinic keratoses should not be treated with Metvixia Cream. The safety and efficacy of Metvixia Cream has not been established in patients with immunosuppression, porphyria or pigmented actinic keratoses.

General

Metvixia Cream Application

During the time period between the application of Metvixia (methyl aminolevulinate) Cream and exposure to red light illumination, the treatment site will become photosensitive. After Metvixia Cream application, patients should avoid exposure of the photosensitive treatment sites to sunlight or bright indoor light (e.g., examination lamps, operating room lamps, tanning beds, or lights at close proximity) during the period prior to red light treatment. Exposure to light may result in a stinging and/or burning sensation and may cause erythema and/or edema of the lesions. Before exposure to sunlight, patients should, therefore, protect treated lesions from the sun by wearing a wide-brimmed hat or similar head covering of light-opaque material. Sunscreens will not protect against photosensitivity reactions caused by visible light. The treated site should be protected from extreme cold with adequate clothing or remaining indoors between application of Metvixia and PDT light treatment.

After illumination of Metvixia Cream, the area treated should be kept covered and away from light for at least 48 hours.

Because of the potential for skin to become photosensitized, the Metvixia Cream should be used by a trained physician to apply drug only to non-hyperkeratotic actinic keratoses and perilesional skin within 5 mm of the lesion. Redness, swelling, burning, and stinging are expected as a result of therapy; however, if these symptoms increase in severity and persist longer than 3 weeks, the patient should contact their doctor.

Metvixia Cream has not been studied for more than two treatment sessions.

Information regarding further treatments for residual or new AK lesions performed after 3 months is not available.

.

Photosensitivity and Device Precautions.

The patient, operator and other persons present should wear protective goggles that sufficiently screen out light with wavelengths from 570 to 670 nm during red light treatment.

If for any reason the patient cannot have the red light treatment after application of Metvixia Cream, the cream should be rinsed off, and the patient should protect the treated area from sunlight, prolonged or intense light for two days. Prolonged exposure for greater than 4 hours to Metvixia Cream should be avoided.

Coagulation defects

Metvixia Cream has not been tested on patients with inherited or acquired coagulation defects.

Hypersensitivity

Metvixia Cream is formulated with refined peanut and almond oil.

Metvixia (methyl aminolevulinate) Cream has not been tested in patients who are allergic to peanuts. Metvixia (methyl aminolevulinate) Cream has demonstrated a high rate of contact sensitization (allergenicity).

Information for Patients

The physician should provide and discuss the attached Patient Package Insert with each patient.

Drug Interactions

There have been no studies of the interaction of Metvixia Cream with any other drugs, including local anesthetics. It is possible that concomitant use of other known photosensitizing agents might increase the photosensitivity reaction of actinic keratoses treated with Metvixia Cream.

Carcinogenesis, Mutagenesis, Impairment to Fertility

Long-term studies to evaluate the carcinogenic potential of Metvixia Cream have not been performed.

Methyl aminolevulinate was negative for genetic toxicity in the Ames assay, and the chromosomal aberration assay in Chinese hamster ovary cells, tested with and without metabolic activation and in the presence and absence of light. Methyl aminolevulinate was also negative in the in vivo micronucleus assay in the rat. In contrast, at least one report in the literature has noted genotoxic effects in cultured rat hepatocytes after aminolevulinate (ALA) exposure with PpIX formation. Other studies have documented oxidative DNA damage in vivo and in vitro as a result of ALA exposure.

No animal fertility studies have been conducted.

Pregnancy

Teratogenic effects

Pregnancy Category C: Animal reproduction studies have not been conducted with Metvixia Cream. It is also not known whether Metvixia Cream can cause fetal harm when administered to a pregnant woman or can affect reproduction capacity.

Metvixia Cream should be given to a pregnant woman only if clearly needed.

Nursing Mothers

The amount of methyl aminolevulinate secreted into human breast milk following topical administration of Metvixia Cream is not known. Because many drugs are secreted in human milk, caution should be exercised when Metvixia Cream is administered to a nursing mother. If Metvixia Cream is used in a nursing mother, a decision should be made whether or not to stop nursing.

Pediatric Use

It is not recommended that Metvixia Cream be used in pediatric patients. Actinic keratosis is rarely found in pediatric patients.

Geriatric Use

Seventy percent (269 among 383) of the patients treated with Metvixia Cream in all clinical studies of actinic keratosis were 65 years of age or older. No overall differences in safety and efficacy were observed between patients aged 65 years and older and those who were younger.

ADVERSE REACTIONS

Dermal Safety Studies

Provocative studies to evaluate irritancy and sensitization have demonstrated that Metvixia Cream is an irritant and sensitizer. A provocative cumulative irritancy and sensitization (allergenicity) study of Metvixia Cream with a cross-sensitization challenge with ALA was performed in 156 subjects. Only 98 of the 156 subjects tested entered the challenge phase. Fifty-two percent of the subjects (30/58), who agreed to challenge with Metvixia Cream, were positive (sensitized). Forty subjects refused challenge with Metvixia Cream and 60 withdrew. At least 58 of the 60 subjects who withdrew from the study discontinued due to irritation/sensitization.

Ninety-eight subjects agreed to challenge with ALA. Two percent of the ALA challenged subjects (2/98) were scored as equivocal reactions and 2% in the paraffin vehicle group were scored as positive.

Adverse Events

In vehicle-controlled phase 3 studies of actinic keratosis, 88% of patients treated with Metvixia Cream reported one or more adverse events.

Burning was the most frequent complaint, reported by 50% of patients (ranging from mild, to severe) and 9% of those patients reported severe burning sensation. Pain in the skin was reported by 21% of patients and 7% had severe pain. Local erythema lasting up to two weeks and edema up to one week after treatment were reported by 31% and 6% of patients.

Symptoms and signs of local phototoxicity were observed in 88% of patients treated with Metvixia Cream in all clinical studies of Metvixia -PDT for actinic keratoses.

Percentage of patients with local adverse reactions based on occurrence per patient in vehicle controlled phase 3 studies.
Events | Metvixia-PDT (n=130) | Vehicle PDT* (n=61)
 | n (%) of patients with AEs | n (%) of patients with AEs
Burning sensation skin | 65 (50.0%) | 9 (14.8%)
Erythema | 60 (46.2%) | 12 (19.7%)
Skin pain | 27 (20.8%) | 6 (9.8%)
Stinging skin | 25 (19.2%) | 2 (3.3%)
Crusting | 20 (15.4%) | 6 (9.8%)
Edema skin | 20 (15.4%) | 1 (1.6%)
Skin peeling | 14 (10.8%) | 2 (3.3%)
Blisters | 14 (10.8%) | 2 (3.3%)
Bleeding skin | 11 (8.5%) | 2 (3.3%)
Pruritus/Itching | 17 (13.1%) | 2 (3.3%)
Skin ulceration | 7 (5.4%) | 0 (0%)
Skin infection | 3 (2.3%) | 1 (1.6%)
Skin hyper-pigmentation | 1 (0.8%) | 0 (0%)

The majority of patients in all the clinical trials had local pain or discomfort upon illumination. There were 4 (1.0%) withdrawals/discontinuations among 383 patients treated with Metvixia Cream in all the clinical trials of actinic keratosis, all of which were due to the adverse event of local pain on illumination.

There have been reported instances of patients treated with Metvixia Cream (2 out of 130) who have developed squamous cell and basal cell carcinoma at the site of treatment. The relationship to treatment with Metvixia Cream is unknown.

Serious erythema and facial edema have been described in European post-marketing reports.

OVERDOSAGE

Metvixia Cream overdose has not been reported. If the patient for any reason cannot have the red light treatment during the prescribed period after application (the 3 hour timespan), the cream should be rinsed off, and the patient should protect the exposed area from sunlight, prolonged or intense light for two days.

Red Light Overdose

There is no information on overdose of red light following Metvixia Cream application.

In case of red light overexposure and skin burn occurs, the patient should be treated according to standard of practice guidelines for treatment of cutaneous burns.

DOSAGE AND ADMINISTRATION

Photodynamic therapy for non-hyperkeratotic actinic keratoses with Metvixia Cream is a multi-stage process as described below: Two treatment sessions 7 days apart should be conducted. Not more than one gram (half a tube) of Metvixia Cream should be applied per treatment session.

One Metvixia -PDT session consists of:

1) Lesion debriding –
Before applying Metvixia Cream, the surface of the lesions should be prepared with a small dermal curette to remove scales and crusts and roughen the surface of the lesion. This is to facilitate access of the cream and light to all parts of the lesion.

Figure 1 A Lesion debriding

Only nitrile gloves should be worn during this and subsequent steps and Universal Precautions should be taken. Vinyl and latex gloves do not provide adequate protection when using this product.

Figure 1B Lesion debriding

2) Application of Metvixia Cream –
Using a spatula, apply a layer of Metvixia Cream about 1 mm thick to the lesion and the surrounding 5 mm of normal skin. Do not apply more than one gram of Metvixia Cream for each patient per treatment session.

Figure 2: Cream application

The area to which the cream has been applied should then be covered with an occlusive, non-absorbent dressing for 3 hours. Multiple lesions may be treated during the same treatment session. Each treatment field is limited to a diameter of 55 mm. Only nitrile gloves should be worn by the qualified healthcare provider in order to avoid skin contact with the cream. This product is not intended for application by patients or unqualified medical personnel.

Figure 3: Occlusive dressing application

3) Wait for 3 hours - (at least 2.5 hours, but no more than 4 hours).
After Cream application, patients should avoid exposure of the photosensitive treatment sites to sunlight or bright indoor light (e.g., examination lamps, operating room lamps, tanning beds, or lights at close proximity) during the period prior to red light treatment. Exposure to light may result in a stinging and/or burning sensation and may cause erythema and/or edema of the lesions. Patients should protect treated areas from the sun by wearing a wide-brimmed hat or similar head covering of light-opaque material. Sunscreens will not protect against photosensitivity reactions caused by visible light. It has not been determined if perspiration can spread the Metvixia Cream outside the treatment site to the eyes or surrounding skin. The treated site should be protected from extreme cold with adequate clothing or remaining indoors between application of Metvixia Cream and PDT light treatment.

4) Removal of Dressing and Rinse Off Excess Cream - Following removal of the occlusive dressing, clean the area with saline and gauze. Nitrile gloves should be worn at this step by the trained physician.

Figure 4: Cream removal

5) Illumination of Metvixia Treated Lesion - It is important to ensure that the correct light dose is administered. The light intensity at the lesion surface should not be higher than 200 mW/cm^2. Patient and operator should adhere to safety instructions and Universal Precautions provided with the lamp. The patient and operator should wear protective goggles during illumination. Patients should be advised that transient stinging and/or burning at the target lesion sites may occur during the period of light exposure.

Figure 5: Illumination

The CureLight BroadBand Model CureLight 01 lamp is approved for the use in Metvixia -PDT. The lamp should be carefully calibrated so that dosing is accurate and immediately thereafter the lesion should be exposed to red light with a continuous spectrum of 570 to 670 nm and a total light dose of 75 J/cm^2. To avoid direct contact between lamp parts and patient skin, always use disposable protective plastic sleeves on the positioning device and on the light measuring probe. Following each patient treatment, the disposable protective plastic sleeves should be removed from the positioning device and from the light measuring probe and discarded.

If red light treatment is interrupted or stopped for any reason, it may be restarted. If the patient for any reason cannot have the red light treatment during the prescribed period after application (the 3 hour timespan), the cream should be rinsed off and the patient should protect the exposed area from sunlight, prolonged or intense light for two days. Metvixia Cream is not intended for use with any device other than the approved lamp: CureLight BroadBand Model CureLight 01.

Use of Metvixia Cream without subsequent red light illumination is not recommended.

No more than 1 gram (half a tube) of product should be used for each of the two weekly treatment sessions. Multiple lesions may be treated during the same treatment session using a total of 1 gram of Metvixia Cream. Lesion response should be assessed 3 months after the last treatment session.

This product is not intended for application by patients or unqualified medical personnel, therefore, this product is only dispensed to physicians.

HOW SUPPLIED

Metvixia Cream, 16.8%, is available as the following:

NDC 63069-401-01, 2 gram aluminum tube, box of 1

Product Package

Keep out of reach of children

For topical use only by physicians in the physician’s office.

Rx Only

Storage Conditions

Store refrigerated, 2-8°C (36-46°F).
Use contents within one week after opening.
Should not be used after 24 hours out of refrigerator.

Metvixia Cream is a registered trade name of PhotoCure ASA.
PhotoCure ASA, Hoffsveien 48, N-0377 Oslo, Norway
USA Contact: Cato Research, Westpark Corporate Center, 4364 South Alston Avenue, Durham NC 27713

Revision: September 5, 2007

SUPPLEMENTAL PATIENT MATERIAL

PATIENT INFORMATION

Metvixia™ Cream 16.8% (phonetic)
Generic name: methyl aminolevulinate hydrochloride

Read this Patient Information before you get treated with Metvixia Cream and each time you get a treatment. There may be new information. This leaflet does not take the place of talking with your doctor about your condition or treatment. Ask your healthcare provider about anything you do not understand about Metvixia Cream.

What is the most important thing I need to know about Metvixia Cream?

- Metvixia Cream with light treatment (Photodynamic therapy or PDT) is only done in medical offices by trained doctors.
- Metvixia Cream is not applied by patients. Metvixia Cream should not be applied by doctors who have not been trained in its use.

What is Metvixia Cream?

Metvixia Cream is a prescription cream used with PDT (light treatment) to treat skin growths on the face and scalp called actinic keratosis (AK). Metvixia Cream is only used for AK skin growths that are thin and not dark colored. AK skin growths are not cancer. AK skin growths are caused partly by too much sun exposure. Metvixia Cream and PDT work together to treat AK skin growths.

Metvixia Cream has not been studied in children for any condition and should not be used in children.

Who should not use Metvixia Cream?

Do not use Metvixia Cream if:

- your skin over reacts to sun or light (photosensitivity)
- you are allergic to porphyrins or to any of the ingredients in Metvixia Cream. The active ingredient is methyl aminolevulinate hydrochloride. Metvixia Cream also contains peanut and almond oil. See the end of this leaflet for a complete list of ingredients in Metvixia Cream.

Before treatment with Metvixia Cream, tell your doctor:

- about your medical conditions, including if you
  - are pregnant or planning to become pregnant. It is not known if Metvixia Cream can harm your unborn baby.
  - are breastfeeding. It is not known if Metvixia Cream passes into your milk and if it can harm your baby. You should decide whether or not to stop breastfeeding while getting treatment with Metvixia Cream. Talk to your doctor for help with this choice.
  - are allergic to nuts or peanuts
  - have or had skin cancer or other skin growths on your body
  - have bleeding problems.
- about all the medicines you take, including prescription and non-prescription medicines, vitamins and herbal supplements. It is not known if Metvixia Cream and other medicines can affect each other.

How should I use Metvixia Cream?

- Metvixia Cream and PDT treatment is only done by trained doctors.
- You will receive 2 treatments with Metvixia Cream and PDT 7 days (1 week) apart. Your doctor will check you three months after treatment to see if the treatment worked for you. (See the end of this leaflet for the section “Treatment with Metvixia Cream and PDT.”)
- Metvixia Cream is for skin use only. Do not get Metvixia Cream in your eyes, mouth, or nose. Tell your doctor right away if this happens.

What should I avoid while using Metvixia Cream?

During the 3 hours that Metvixia Cream is on your skin:

- Avoid exposure to sunlight or bright indoor light during the 3 hours that Metvixia Cream is on your skin. Wear a protective hat and clothing if you need to be outside in the sun.
- Avoid exposure to cold temperatures during the 3 hours that Metvixia Cream is on your skin. Wear warm clothing and keep your treated skin site covered if you are in cold temperatures.

If for some unavoidable reason you are not treated with the lamp you should

- Carefully rinse off the Cream.
- Avoid exposure to sunlight, prolonged or intense light for two days after treatment.

What are the possible side effects of Metvixia Cream with PDT treatment?

Common side effects of Metvixia Cream with PDT treatment include the following skin reactions at the treated site:

- burning feeling
- redness
- pain
- stinging
- swelling
- crusting, peeling, blisters, bleeding, itching, ulcers
- infection

Tell your doctor if you get any of these side effects. Your healthcare provider should be able to treat these reactions according to standard treatments for such skin reactions. These reactions usually go away within 10 days of treatment. Redness may last for up to 1 month. If any of your skin reactions get worse and last longer than 3 weeks, call your doctor.

These are not all the side effects of Metvixia Cream with PDT. Ask your doctor or pharmacist for more information.

General information about Metvixia Cream

Medicines are sometimes prescribed for conditions that are not mentioned in patient information leaflets.

This leaflet summarizes the most important information about Metvixia Cream. If you would like more information, talk with your doctor. You can ask your doctor for information about Metvixia Cream that is written for health professionals.

Toll-free number and/or website will be provided when available for the US market.

What are the ingredients in Metvixia Cream?

Active Ingredient: methyl aminolevulinate hydrochloride

Other Ingredients: Glyceryl monostearate, cetostearyl alcohol, poloxyl stearate, cholesterol, oleyl alcohol glycerin, white petrolatum, isopropyl myristate, refined peanut oil, refined almond oil, edetate disodium, methylparaben and propylparaben. The color of the product is cream to pale yellow.

Treatment with Metvixia Cream and PDT

Figure 1: Lesion debriding

Your doctor will prepare your skin by gently scraping (debriding) your skin growths before treating with Metvixia Cream and PDT. A small skin scraper is used to remove scales and crusts and to roughen the surface of any skin growths. This is to help Metvixia Cream and PDT to reach all parts of the skin growths.

Figure 2: Cream application

Metvixia Cream is applied to the actinic keratosis skin growths and to a small area of the skin around the growths.

Figure 3: Clear bandage application

The treated skin areas will be covered with a special clear bandage for about 3 hours.

During these 3-hours you should avoid exposure of treated area to sunlight or bright indoor light. Exposure to light may make your treated skin area sting or burn. Your treated skin area may turn red or swell (photosensitive reactions). Wear a hat and protective clothes if you are exposed to sunlight during this time. Sunscreens will not help protect your treated skin during this time. In cold weather, your treated skin site should be protected from the cold with warm clothes or you should stay indoors for these 3 hours between the cream and light treatment.

Figure 4: Cream removal

The clear bandage will be removed and the area will be rinsed with a saline solution before the PDT (light) treatment.

Figure 5: Illumination

The skin growth will be treated with PDT. PDT lasts about 10 minutes for each area treated with the lamp. You will wear protective goggles to cover your eyes during this part of the treatment.

More than 1 skin growth may be treated at a time. Your treated skin areas may burn, feel painful, sting, or tingle during light treatment. These symptoms may last for a few hours after the treatment. If you cannot have the light treatment 3 hours after Metvixia Cream is applied, rinse the cream off your skin and you must protect your skin from sunlight and bright indoor light for 2 days.

This product should only be stored in refrigerators in pharmacies and medical offices.

Rx only

Metvixia Cream is a registered trade name of PhotoCure ASA.
Sponsor: PhotoCure ASA, Hoffsveien 48, NO-0377 Oslo, Norway
U.S. Contact: Cato Research, Westpark Corporate Center, 4364 South Alston Avenue, Durham NC 27713
Manufacturer: Penn Pharmaceutical Services Ltd., Tafarnaubach Industrial Estate, Tredegar, Gwent, NP22 3AA, UK.